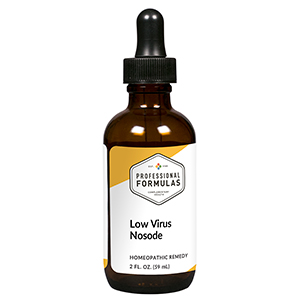 DRUG LABEL: Low Virus Nosode
NDC: 63083-4023 | Form: LIQUID
Manufacturer: Professional Complementary Health Formulas
Category: homeopathic | Type: HUMAN OTC DRUG LABEL
Date: 20190815

ACTIVE INGREDIENTS: COXSACKIEVIRUS A21 12 [hp_X]/59 mL; HUMAN HERPESVIRUS 5 12 [hp_X]/59 mL; HUMAN HERPESVIRUS 4 12 [hp_X]/59 mL; HAEMOPHILUS INFLUENZAE 12 [hp_X]/59 mL; DALEA FOLIOLOSA WHOLE 12 [hp_X]/59 mL; DRABA VERNA WHOLE 12 [hp_X]/59 mL; JUSTICIA SPICIGERA LEAF 12 [hp_X]/59 mL; VACCINIA VIRUS STRAIN NEW YORK CITY BOARD OF HEALTH LIVE ANTIGEN 12 [hp_X]/59 mL; HUMAN VARICELLA-ZOSTER IMMUNE GLOBULIN 12 [hp_X]/59 mL; BACILLUS CALMETTE-GUERIN LIVE ANTIGEN, UNSPECIFIED SUBSTRAIN 30 [hp_X]/59 mL; POLIOVIRUS TYPE 1 ANTIGEN (FORMALDEHYDE INACTIVATED) 30 [hp_X]/59 mL
INACTIVE INGREDIENTS: ALCOHOL; WATER

N23

ACTIVE INGREDIENTS

Coxsackievirus 12X
Cytomegalovirus 12X
Epstein-Barr virus 12X
Haemophilus influenzae 12X
Roseola 12X
Rubella 12X
Scarlatina 12X
Vaccinotoxinum 12X
Varicella 12X
BCG 30X
Poliomyelitis 30X

QUESTIONS

Professional Formulas

PO Box 2034 Lake Oswego, OR 97035

INDICATIONS

Temporarily relieves fatigue, sore throat, minor aches and pains in the muscles or joints, occasional headache, chills, sweats, cough, nausea or vomiting, or abdominal discomfort.*

PURPOSE

*Claims based on traditional homeopathic practice, not accepted medical evidence. Not FDA evaluated.

WARNINGS

Persistent symptoms may be a sign of a serious condition. If symptoms persist or are accompanied by a fever, rash, or persistent headache, consult a doctor. Keep out of the reach of children. In case of overdose, get medical help or contact a poison control center right away. If pregnant or breastfeeding, ask a healthcare professional before use.

Keep out of the reach of children.

PREGNANCY OR BREAST FEEDING

If pregnant or breastfeeding, ask a healthcare professional before use.

DIRECTIONS

Place drops under tongue 30 minutes before/after meals. Adults and children 12 years and over: Take 10 to 15 drops once weekly or monthly. If mild symptoms are present, take 10 drops up to 3 times per day. Consult a physician for use in children under 12 years of age.

OTHER INFORMATION

Tamper resistant. If seal is broken, do not use. After opening, close container tightly and store at room temperature away from heat.

INACTIVE INGREDIENTS

20% ethanol, purified water.

LABEL

Est 1985

Professional Formulas

Complementary Health

Low Virus Nosode

Homeopathic Remedy

2 FL. OZ. (59 mL)